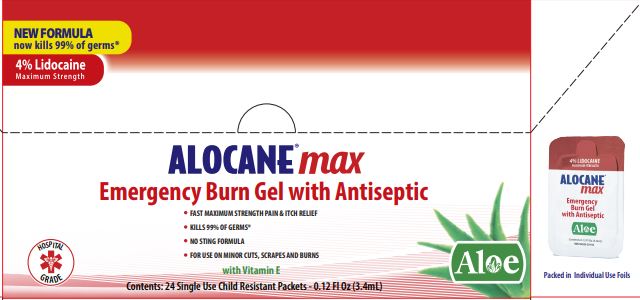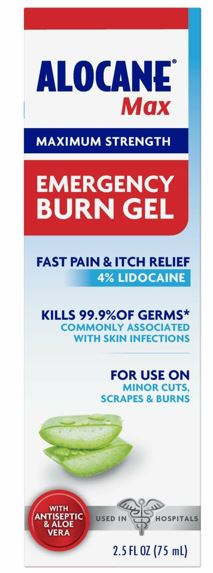 DRUG LABEL: Alocane Max
NDC: 68229-406 | Form: GEL
Manufacturer: Quest Products LLC
Category: otc | Type: HUMAN OTC DRUG LABEL
Date: 20251204

ACTIVE INGREDIENTS: LIDOCAINE HYDROCHLORIDE 4 g/100 mL; BENZALKONIUM CHLORIDE 0.13 g/100 mL
INACTIVE INGREDIENTS: SODIUM HYDROXIDE; PROPANEDIOL; ALOE VERA LEAF; DIMETHYL ISOSORBIDE; HYDROXYETHYL CELLULOSE (5500 MPA.S AT 2%); PHENOXYETHANOL; .ALPHA.-TOCOPHEROL ACETATE; WATER; ETHYLHEXYLGLYCERIN; EDETATE DISODIUM

Alocane® Max gel

Active Ingredients

Benzalkonium Chloride 0.13%

Lidocaine HCl 4.0%

Purpose

First Aid Antiseptic

External Analgesic

Uses:

First aid to help prevent bacterial infection associated with contamination or skin infection, and for the temporary relief of pain and itching associated with minor: :

- Burns
- Cuts
- Sunburn
- Scrapes
- Minor Skin Irritations

Warnings

For external use only.

Ask a doctor before use if you have:

- Deep or puncture wounds
- Animal bites
- Serious burns

Do not use:

- In or near the eyes
- In large quantities or over large areas of the body
- On raw surfaces or blistered areas

Stop use and ask doctor: If condition worsens, or if symptoms persist for more than 7 days or clear up and occur again within a few days.

PREGNANCY OR BREAST FEEDING

If pregnant or breast-feeding, ask a health care professional before use.

Keep out of reach of children. If swallowed, get medical help or call a Poison Control Center right away.

Directions:

Adults and children 2 years of age and older: Clean the affected area. Apply a small amount of gel on the affected area not more than 3 to 4 times daily. May be covered with a sterile bandgae (let dry first).

Children under 2 years of age: ask a doctor.

Other Information

Store at room temperature 15°-30°C (59°-86°F)

Inactive Ingredients

Aloe Barbadensis (Aloe) Leaf Juice, Dimethyl Isosorbide, Disodium EDTA, Ethylhexyglycerin, Hydroxyethyl Cellulose, Phenoxyethanol, Propanediol, Sodium Hydroxide, Tocopheryl Acetate (Vitamin E), Water.